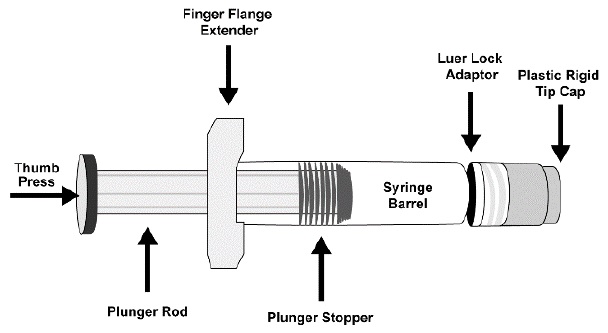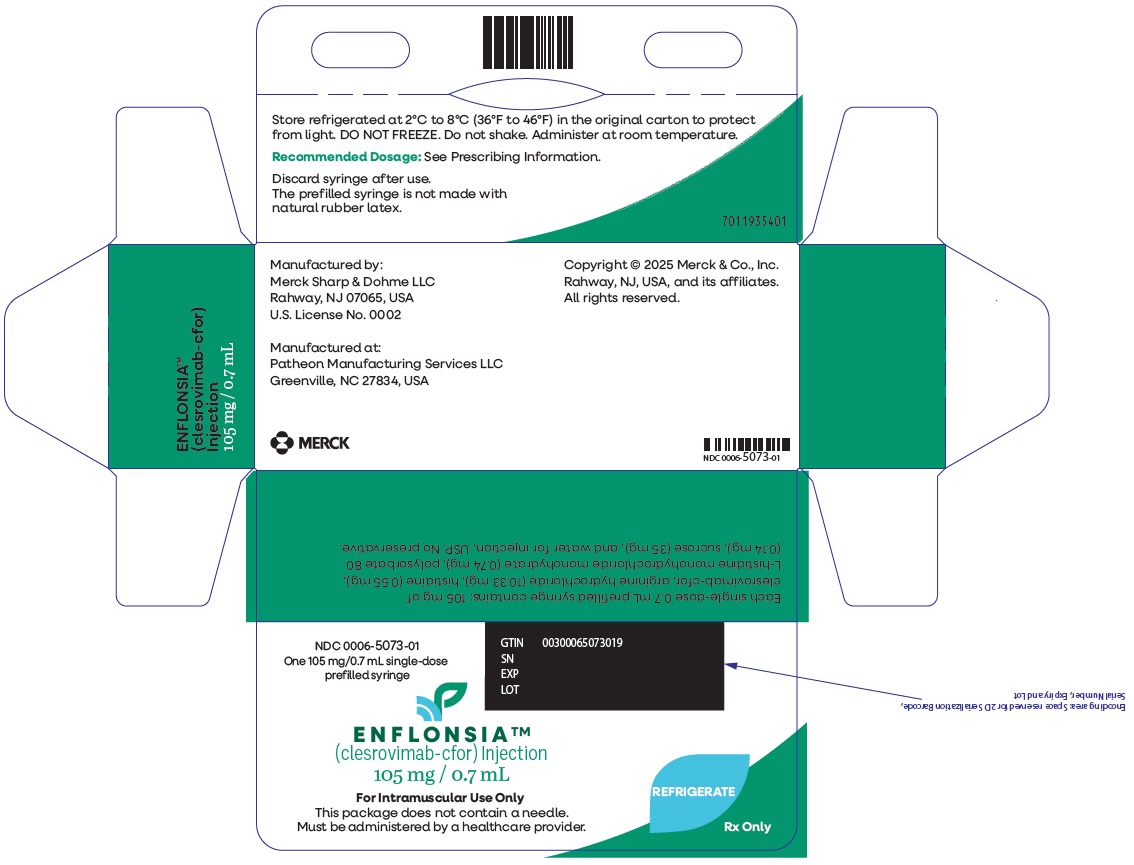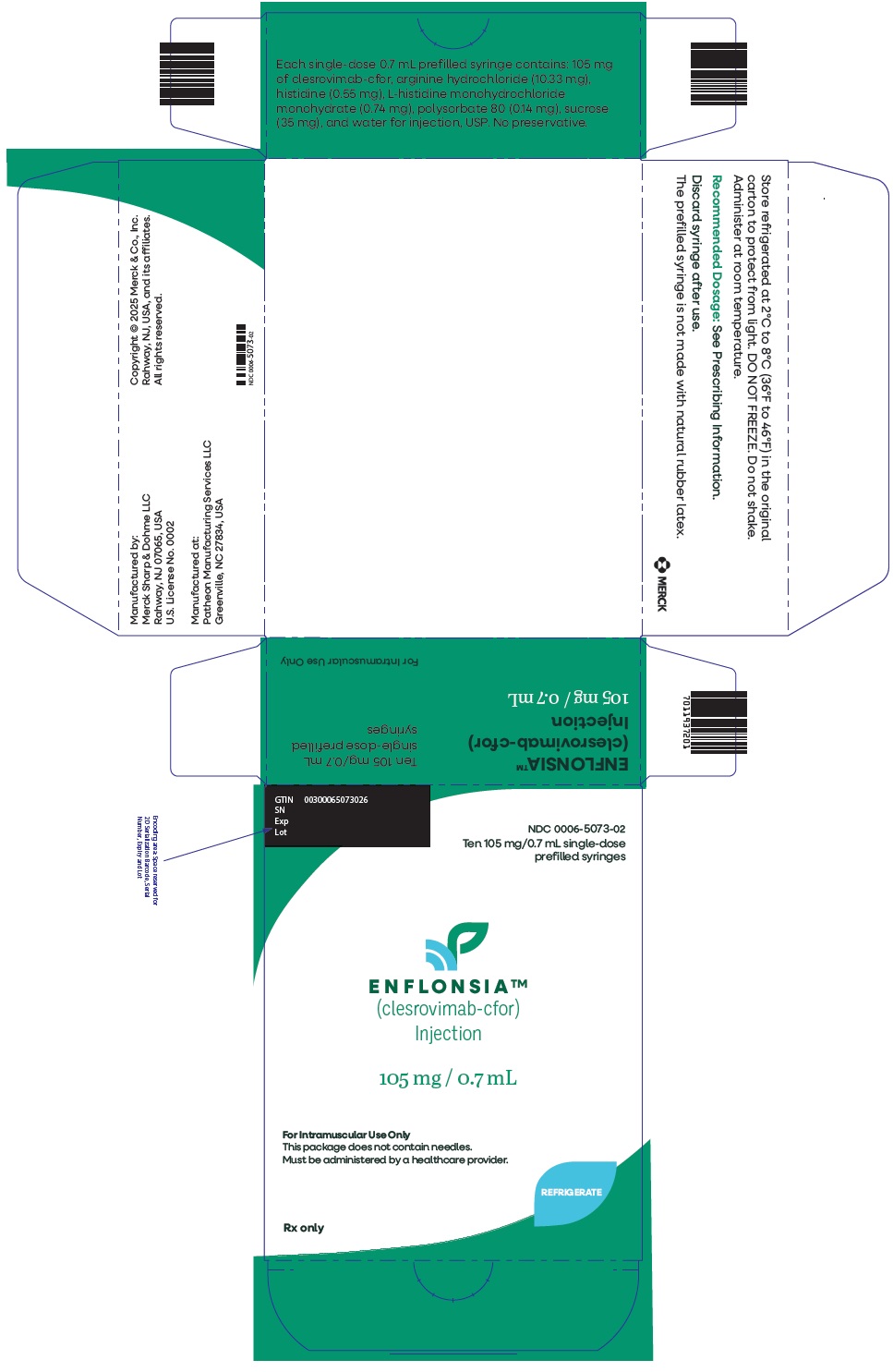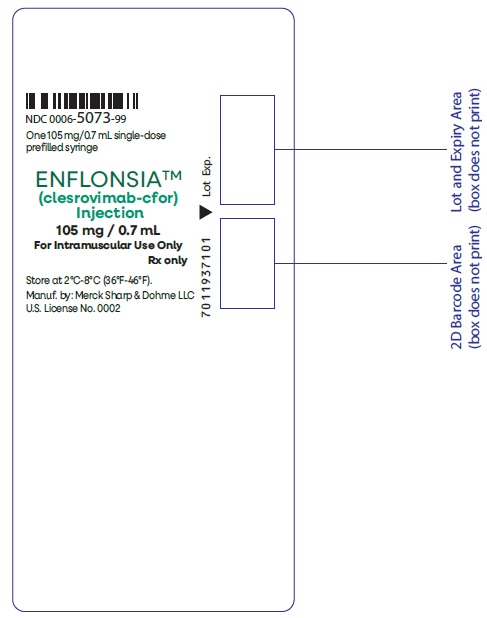 DRUG LABEL: ENFLONSIA
NDC: 0006-5073 | Form: INJECTION, SOLUTION
Manufacturer: Merck Sharp & Dohme LLC
Category: prescription | Type: HUMAN PRESCRIPTION DRUG LABEL
Date: 20250620

ACTIVE INGREDIENTS: CLESROVIMAB 150 mg/1 mL
INACTIVE INGREDIENTS: ARGININE HYDROCHLORIDE; HISTIDINE HYDROCHLORIDE MONOHYDRATE; HISTIDINE; POLYSORBATE 80; SUCROSE; WATER

HIGHLIGHTS OF PRESCRIBING INFORMATION

These highlights do not include all the information needed to use ENFLONSIA safely and effectively. See full prescribing information for ENFLONSIA.
ENFLONSIA™ (clesrovimab-cfor) injection, for intramuscular use
Initial U.S. Approval: 2025

1 INDICATIONS AND USAGE

ENFLONSIA is a respiratory syncytial virus (RSV) F protein-directed fusion inhibitor indicated for the prevention of RSV lower respiratory tract disease in neonates and infants who are born during or entering their first RSV season. (1)

2 DOSAGE AND ADMINISTRATION

Recommended dosage: 105 mg administered as a single intramuscular (IM) injection. (2.1)

3 DOSAGE FORMS AND STRENGTHS

Injection: 105 mg/0.7 mL in a single-dose prefilled syringe. (3)

4 CONTRAINDICATIONS

ENFLONSIA is contraindicated in infants with a history of serious hypersensitivity reactions, including anaphylaxis, to any component of ENFLONSIA. (4)

5 WARNINGS AND PRECAUTIONS

Hypersensitivity Including Anaphylaxis: Serious hypersensitivity reactions, including anaphylaxis, have been observed with other human immunoglobulin G1 (IgG1) monoclonal antibodies. Initiate appropriate medications and/or supportive care if such reactions occur. (5.1)

6 ADVERSE REACTIONS

Most common adverse reactions were injection-site erythema (3.8%), injection-site swelling (2.7%) and rash (2.3%). (6.1)

To report SUSPECTED ADVERSE REACTIONS, contact Merck Sharp & Dohme LLC at 1-877-888-4231 or FDA at 1-800-FDA-1088 or www.fda.gov/medwatch.

8 USE IN SPECIFIC POPULATIONS

The safety and effectiveness of ENFLONSIA have not been established in children older than 12 months of age. (8.4)

FULL PRESCRIBING INFORMATION

1 INDICATIONS AND USAGE

ENFLONSIA is indicated for the prevention of respiratory syncytial virus (RSV) lower respiratory tract disease in neonates and infants who are born during or entering their first RSV season.

2 DOSAGE AND ADMINISTRATION

2.1 Recommended Dosage

The recommended dose for neonates and infants born during or entering their first RSV season is 105 mg administered as a single intramuscular (IM) injection.

For neonates and infants born during the RSV season, administer ENFLONSIA once starting from birth. For infants born outside the RSV season, administer ENFLONSIA once prior to the start of their first RSV season considering the duration of protection provided by ENFLONSIA [see Clinical Pharmacology (12.2)].

Infants Undergoing Cardiac Surgery with Cardiopulmonary Bypass

For infants undergoing cardiac surgery with cardiopulmonary bypass during or entering their first RSV season, an additional 105 mg dose administered as an IM injection is recommended as soon as the infant is stable after surgery to ensure adequate clesrovimab-cfor serum levels.

2.2 Administration Instructions

ENFLONSIA must be administered by a healthcare provider.

Before injection, remove ENFLONSIA from the refrigerator and allow the prefilled syringe to come to room temperature for approximately 15 minutes. Parenteral drug products should be inspected visually for particulate matter and discoloration prior to administration, whenever solution and container permit. ENFLONSIA is a clear to slightly opalescent, colorless to slightly yellow solution. This product should not be used if particulate matter or discoloration is found. Do not use if the prefilled syringe has been dropped or damaged, the security seal on the carton has been broken, or the expiration date has passed. Refer to Figure 1 for prefilled syringe components.

Figure 1: Prefilled Syringe Components

Step 1: Hold the syringe barrel in one hand and unscrew the tip cap by twisting it counter-clockwise with the other hand. Do not remove the Luer Lock adaptor and the finger flange extender.

Step 2: Attach a sterile Luer Lock needle by twisting in a clockwise direction until the needle fits securely on the syringe. Due to the viscosity of the product, use a 22- to 25-gauge needle.

Step 3: Inject the entire contents of the ENFLONSIA prefilled syringe intramuscularly in the anterolateral aspect of the thigh. ENFLONSIA should not be injected in the gluteal area or areas where there may be a major nerve trunk and/or blood vessel.

Step 4: Discard syringe into a sharps container.

Co-administration with Childhood Vaccines and Immunoglobulin Products
ENFLONSIA can be given concomitantly with childhood vaccines [see Clinical Pharmacology (12.3)]. When ENFLONSIA is administered concomitantly with injectable vaccines, it should be given using a separate syringe and at a different injection site. Do not mix ENFLONSIA with any vaccines or medications in the same syringe or vial.

There is no information regarding co-administration of ENFLONSIA with other immunoglobulin products. There are no data regarding substitution of ENFLONSIA for palivizumab once prophylaxis treatment is initiated with palivizumab for the RSV season.

3 DOSAGE FORMS AND STRENGTHS

Injection: 105 mg/0.7 mL clear to slightly opalescent, colorless to slightly yellow solution in a single-dose prefilled syringe.

4 CONTRAINDICATIONS

ENFLONSIA is contraindicated in infants with a history of serious hypersensitivity reactions, including anaphylaxis, to any component of ENFLONSIA [see Warnings and Precautions (5.1) and Description (11)].

5 WARNINGS AND PRECAUTIONS

5.1 Hypersensitivity Including Anaphylaxis

Serious hypersensitivity reactions, including anaphylaxis, have been observed with other human immunoglobulin G1 (IgG1) monoclonal antibodies. If signs or symptoms of a clinically significant hypersensitivity reaction or anaphylaxis occur, initiate appropriate medications and/or supportive therapy.

5.2 RSV Diagnostic Test Interference

Clesrovimab-cfor may interfere with some immunologically-based RSV diagnostic assays (i.e., rapid antigen tests) as observed in laboratory studies. Confirmation using a reverse transcriptase polymerase chain reaction (RT-PCR) assay is recommended when rapid antigen assay results are negative and clinical observations are consistent with RSV infection [see Drug Interactions (7.1)].

6 ADVERSE REACTIONS

6.1 Clinical Trials Experience

Because clinical trials are conducted under widely varying conditions, adverse reaction rates observed in the clinical trials of a drug cannot be directly compared to rates in the clinical trials of another drug and may not reflect the rates observed in practice.

The safety of ENFLONSIA was evaluated in 2,858 infants who received ENFLONSIA in Phase 2b/3 and Phase 3 clinical trials (Trial 004 and Trial 007).

Neonates and Infants Entering Their First RSV Season (Trial 004)

Trial 004 was a Phase 2b/3, randomized, double-blind placebo-controlled, multisite trial conducted in early and moderate preterm infants (≥29 to <35 weeks gestational age (GA)) and late preterm and full-term infants (≥35 weeks GA). Participants were randomized 2:1 and received a single 105 mg dose of ENFLONSIA (N=2,412, including 422 early and moderate preterm infants) or saline placebo (N=1,202, including 209 early and moderate preterm infants) by IM injection. Participants were monitored for 30 minutes post-dose. Safety was assessed using an electronic diary device from Days 1 through 42 post-dose. Participants were monitored for serious adverse events (SAEs) through the duration of their participation for up to 365 days post-dose. A subset of participants was monitored for SAEs for up to 515 days post-dose.

Table 1 summarizes the adverse reactions in participants who received ENFLONSIA. Most (≥97%) of the adverse reactions were toxicity grade 1 (mild) or grade 2 (moderate).

Table 1: Adverse Reactions Reported at an Incidence Higher Than Placebo (Trial 004)
Adverse Reaction | ENFLONSIA N=2,412 [Sample size reflects the number of participants included in the safety analysis population.] % | Placebo N=1,202 %
Injection-site erythema [Solicited on Day 1 through Day 5 post-dose using an electronic diary device.] (occurring within 5 days post-dose) | 3.8 | 3.3
Injection-site swelling (occurring within 5 days post-dose) | 2.7 | 2.6
Rash [Defined by the following grouped preferred terms: rash, rash erythematous, rash macular, rash papular, rash maculo-papular, rash vesicular, rash exfoliative, dermatitis allergic, drug eruption and toxic skin eruption.] (occurring within 14 days post-dose) | 2.3 | 1.9

Infants Born at ≤35 Weeks Gestational Age and Infants with Chronic Lung Disease (CLD) of Prematurity or Hemodynamically Significant Congenital Heart Disease (CHD) Entering Their First RSV Season (Trial 007)

Trial 007 was a Phase 3, randomized, partially-blind, palivizumab-controlled, multisite trial conducted in infants at increased risk of severe RSV disease. Participants were randomized and received a single 105 mg dose of ENFLONSIA (N=446) followed by a dose of placebo one month later or 3 to 5 monthly doses of 15 mg/kg palivizumab (N=450) by IM injection. Of the 446 participants who received ENFLONSIA, 176 had CLD of prematurity or CHD and 270 were early or moderate preterm infants (≤35 weeks GA) without CLD of prematurity or CHD. Participants were monitored for 30 minutes post-dose. Safety was assessed using an electronic diary device from Day 1 (dose 1) through 14 days post-dose 2, and 14 days after each subsequent dose. Participants were monitored for serious adverse events in the first RSV season for up to 365 days.

The safety profile of ENFLONSIA in infants at increased risk of severe RSV disease entering their first season was similar to palivizumab and consistent with the safety profile of ENFLONSIA in infants in Trial 004.

7 DRUG INTERACTIONS

7.1 Interference with Rapid Antigen Detection RSV Diagnostic Assays

Clesrovimab-cfor may interfere with some immunologically-based RSV diagnostic assays (i.e., rapid antigen tests) as observed in laboratory studies. Confirmation using an RT-PCR assay is recommended when rapid antigen RSV diagnostic assay results are negative and clinical observations are consistent with RSV infection. Clesrovimab-cfor does not interfere with RT-PCR diagnostic assays [see Warnings and Precautions (5.2)].

8 USE IN SPECIFIC POPULATIONS

8.1 Pregnancy

ENFLONSIA is not indicated for use in females of reproductive potential.

8.2 Lactation

ENFLONSIA is not indicated for use in females of reproductive potential.

8.4 Pediatric Use

The safety and effectiveness of ENFLONSIA have been established for the prevention of RSV lower respiratory tract disease in neonates and infants born during or entering their first RSV season and the information on this use is discussed throughout the labeling.

The safety and effectiveness of ENFLONSIA have not been established in children older than 12 months of age.

10 OVERDOSAGE

There is limited experience of overdose with ENFLONSIA. There is no specific treatment for an overdose with ENFLONSIA. In the event of an overdose, the infant should be monitored for the occurrence of adverse reactions and provided with symptomatic treatment as appropriate.

11 DESCRIPTION

Clesrovimab-cfor is a respiratory syncytial virus F protein-directed fusion inhibitor. Clesrovimab-cfor is a fully human immunoglobulin G1 kappa (IgG1κ) monoclonal antibody produced in recombinant Chinese hamster ovary (CHO) cells. The molecular weight is approximately 149 kDa.

ENFLONSIA (clesrovimab-cfor) injection is a sterile, preservative-free, clear to slightly opalescent, colorless to slightly yellow solution for intramuscular injection.

Each 0.7 mL contains 105 mg of clesrovimab-cfor, arginine hydrochloride (10.33 mg), histidine (0.55 mg), L-histidine monohydrochloride monohydrate (0.74 mg), polysorbate 80 (0.14 mg), sucrose (35 mg) and water for injection (USP). The pH is 6.0.

12 CLINICAL PHARMACOLOGY

12.1 Mechanism of Action

ENFLONSIA is a monoclonal antibody with anti-RSV activity [see Microbiology (12.4)].

12.2 Pharmacodynamics

RSV serum neutralizing antibody titer correlates with clesrovimab-cfor serum concentration. Following IM administration of clesrovimab-cfor in infants, the RSV neutralizing antibody titers in serum were estimated to be approximately 7 times higher than baseline at 4 hours after clesrovimab-cfor dosing and maximum titers were reached by day 7, for a typical infant weighing 5 kg.

Exposure-Response Relationship
In the Phase 2b/3 trial evaluating the recommended dose of clesrovimab-cfor (a single dose of 105 mg) in healthy preterm and full-term infants (Trial 004), no significant relationship was observed between AUC (from day 1 to day 150) and clinical outcomes (e.g., RSV-associated Medically Attended Lower Respiratory Infection (MALRI)).

Duration of Protection
Based on clinical trial data, the duration of protection demonstrated by a single dose of ENFLONSIA extends through 5 months [see Clinical Studies (14.2)].

12.3 Pharmacokinetics

The PK of clesrovimab-cfor is approximately dose-proportional following a single IM administration of doses ranging from 20 mg to 210 mg in infants. Following IM administration of the 105 mg recommended dose, the geometric mean (% geometric CV) area under the time concentration curve from day 1 to day 150 (AUC0-150) is 6,470 mcg×d/mL (22.6%), peak concentration (Cmax) is 120 mcg/mL (25.4%), and the concentration at day 150 (C150) is 10.3 mcg/mL (36.6%). In the first RSV season, the clesrovimab-cfor serum exposures were similar in neonates and infants in Trial 004, in preterm neonates and infants born at less than or equal to 35 weeks GA (including less than 29 weeks GA) in Trial 007, and in neonates and infants with CLD or CHD in Trial 007.

Absorption

The median time to maximum concentration is 6.5 days (5.9, 7.4 which are the 2.5 and 97.5 percentiles, respectively).

Distribution

The estimated apparent volume of distribution for clesrovimab-cfor is 830 mL, for a typical infant weighing 5 kg.

Elimination

The clesrovimab-cfor terminal half-life is approximately 44.0 days and the estimated apparent clearance is 19.7 mL/day for a typical infant weighing 5 kg.

Metabolism

Clesrovimab-cfor is degraded into small peptides by catabolic pathways.

Specific Populations

No clinically significant differences in the pharmacokinetics of clesrovimab-cfor were observed based on race or vulnerability to severe RSV disease (i.e., CLD, CHD, or GA <29 weeks). An effect of renal or hepatic impairment on clesrovimab-cfor pharmacokinetics is not expected.

Drug Interaction Studies

Since clesrovimab-cfor is eliminated by catabolism, no metabolic drug-drug interactions are expected. However, no formal drug interaction studies have been performed with ENFLONSIA.

Clinical Studies

Vaccines:
In clinical trials, when ENFLONSIA was given concomitantly with routine childhood vaccines, the safety profile of the co-administered regimen was generally comparable to the safety profile when ENFLONSIA and childhood vaccines were administered alone.

12.4 Microbiology

Mechanism of Action

Clesrovimab-cfor is a recombinant human immunoglobulin G1 kappa (IgG1κ) neutralizing monoclonal antibody with a YTE triple amino acid substitution (M252Y/S254T/T256E) in the Fc region which increases binding to the neonatal Fc receptor leading to an extended serum half-life. Passive immunity is provided by clesrovimab-cfor, which targets the extracellular domain of the RSV fusion (F) protein to prevent fusion of the viral and cellular membranes and viral entry.

Clesrovimab-cfor binds to a conserved epitope on antigenic site IV on the F protein and binds to RSV A pre-fusion F glycoprotein and post-fusion F glycoprotein with equilibrium dissociation constant values (KD) of 71 pM and 480 pM, respectively.

Antiviral Activity

A neutralization assay in Hep-2 cells was used to determine clesrovimab-cfor potency against RSV A and RSV B isolates. Clesrovimab-cfor neutralized 47 RSV clinical isolates collected from North America locations between 1987 and 2016, with median EC50 values for RSV A isolates of 25 pM (3.71 ng/mL) (n=24; range of 1.2 to 74 pM [0.18 to 11.11 ng/mL]), and for RSV B isolates of 30 pM (4.48 ng/mL) (n=23; range of 4 to 198 pM [0.59 to 29.65 ng/mL]).

Clesrovimab-cfor also neutralized 12 contemporary isolates isolated from Texas, US, between 2016 and 2021, with a median EC50 value for RSV A isolates of 121 pM (18.02 ng/mL) (n=6; range of 59 to 186 pM [8.79 to 27.74 ng/mL]), and for RSV B isolates of 130 pM (19.41 ng/mL) (n=6; range of 95 to 153 pM [14.22 to 22.92 ng/mL]). The relatively high EC50 values for contemporary isolates compared with historical isolates is thought to be related to assay differences because the values for the control viruses also increased.

Antiviral Resistance

In Cell Culture

Clesrovimab-resistant RSV variants were identified after serial passage in cell culture of RSV A or RSV B in the presence of clesrovimab-cfor. Four variants were generated after 6 passages with RSV A, and one variant after 9 passages of RSV B. These variants each had reduced susceptibility to clesrovimab-cfor of >3,800-fold (RSV A) or >360-fold (RSV B) when assessed in cell culture, and harbored the following clesrovimab-cfor binding site substitutions: G446E, S443P+K445N, S443P+G446E, or S443P for the four RSV A variants, respectively, and S443P substitution for the RSV B variant.

In Surveillance Trials

In sequences reported in the GenBank® database (accessed April 15, 2024), the RSV binding epitope for clesrovimab-cfor was highly conserved (99.8%), with 13 polymorphisms identified at contact residues. Of these polymorphisms, the most common (I432T, 0.04% of sequences) conferred 4-fold (RSV A) or 1.6-fold (RSV B) reductions in susceptibility to clesrovimab-cfor in a cell culture neutralization assay. One polymorphism seen in 3 RSV A sequences, G446E, is a resistance-associated substitution selected in cell culture.

In a global surveillance study conducted between 2019 and 2023 in 8 countries across Northern and Southern Hemispheres, the clesrovimab-cfor binding site was highly conserved (>99%) in 300 RSV A and 255 RSV B sequences in clinical samples collected from individuals of various ages (<1 year to >60 years of age).

In Clinical Trials

In Trial 004, more substitutions in the clesrovimab-cfor binding site (amino acid positions 426 to 447) were observed at ≥3% variant allele frequency (VAF) in RSV infections of clesrovimab-cfor-treated participants (15/156 [9.6%]) compared with placebo participants (2/150 [1.3%]) from Day 1 through 180 post-dose. The majority of the binding site substitutions affected residue G446 (RSV A: G446E, G446R or G446W; and RSV B: G446E or G446R), and were seen at >50% VAF in at least one participant each. G446E, G446R, and G446W substitutions are resistance-associated, with G446E and G446W conferring >2,941-fold (RSV A) or >1,299-fold (RSV B) loss of susceptibility to clesrovimab-cfor, and G446R conferring >1,563-fold (RSV A) loss of susceptibility to clesrovimab-cfor (RSV B not assessed). Other binding site substitutions seen in clesrovimab-cfor-treated participants at <10% VAF were RSV B: F435S, S443L, G446V, and V447I (no cell culture neutralization data available).

In Trial 007, RSV infections with binding site substitutions at >50% VAF included RSV A (G446W) and RSV B (G446E and G446R), in clesrovimab-cfor-treated participants.

For Trials 004 and 007, there was no clear association of binding site substitutions seen in RSV infections and RSV-associated Medically Attended Lower Respiratory Infection (MALRI) or hospitalization. However, for substitutions seen at high VAF% from Days 1 to 150 post-dose, one participant in Trial 004 with RSV A G446W substitution had RSV-associated hospitalization, and one participant in Trial 007 with RSV B G446R substitution had RSV-associated severe MALRI and hospitalization.

Cross-resistance

No cross-resistance was seen for RSV variants harboring palivizumab or nirsevimab resistance-associated substitutions in cell culture neutralization assays. Clesrovimab-cfor did not lose activity against RSV A or RSV B clinical isolates with palivizumab resistance-associated substitution N262Y, or recombinant RSV B with nirsevimab resistance-associated substitutions N208S, I64T+K68E, or I64T+K68E+I206M+Q209R, which were observed in clinical trials of nirsevimab. Not all nirsevimab resistance-associated substitutions have been assessed for cross-resistance with clesrovimab-cfor. Both nirsevimab and palivizumab neutralized RSV A and B variants harboring clesrovimab-cfor resistance-associated substitutions G446E or G446W in cell culture.

12.6 Immunogenicity

The observed incidence of anti-drug antibodies (ADA) is highly dependent on the sensitivity and specificity of the assay. Differences in assay methods preclude meaningful comparisons of the incidence of ADA in the studies described below with the incidence of ADA in other studies.

In Trial 004 and Trial 007, after receiving the approved recommended dose in RSV season 1, 6% (120/2112) and 5% (13/291) of participants were ADA-positive on Day 150, respectively; and 12% (124/1033) and 13% (34/261) of participants were ADA-positive through Day 240, respectively.

The impact of ADA on efficacy is unknown due to the low rates of MALRI and ADA. There was no identified impact of ADA on pharmacokinetics, RSV serum neutralizing activity or safety of ENFLONSIA during RSV season 1.

13 NONCLINICAL TOXICOLOGY

13.1 Carcinogenesis, Mutagenesis, Impairment of Fertility

Carcinogenesis, mutagenesis and reproductive toxicity studies have not been performed with ENFLONSIA.

14 CLINICAL STUDIES

14.1 Description of Clinical Trials

The efficacy and safety of ENFLONSIA were evaluated in preterm and full-term infants in the trials summarized in Table 2.

Table 2: Trials Conducted with ENFLONSIA for the Prevention of Medically Attended RSV Lower Respiratory Tract Disease
Trial | Study Population | Study Arms [Participants randomized and treated]
Trial 004 (NCT04767373) | Infants born at ≥29 weeks GA from birth up to 1 year entering their first RSV season. | ENFLONSIA (N=2,411) Placebo (N=1,203) [1 participant was randomized to placebo but received ENFLONSIA]
Trial 007 (NCT04938830) | Infants born at ≤35 weeks GA, or infants with CLD of prematurity or hemodynamically significant CHD from birth up to 1 year entering their first RSV season. | ENFLONSIA (N=446) Palivizumab (N=450)
GA=gestational age; CLD=chronic lung disease; CHD=hemodynamically significant congenital heart disease

14.2 Prevention of RSV-Associated Disease in Neonates and Infants (≥29 Weeks GA) Entering Their First RSV Season (Trial 004)

Trial 004 was a Phase 2b/3, randomized, double-blind placebo-controlled, multi-site trial conducted in 22 countries from the Northern and Southern Hemispheres to evaluate the efficacy of ENFLONSIA in early and moderate preterm infants (≥29 to <35 weeks GA) and late preterm and full-term infants (≥35 weeks GA). The trial assessed the efficacy of ENFLONSIA in the prevention of RSV-associated disease across a spectrum of severity. Participants were randomized 2:1 to receive a single 105 mg dose of ENFLONSIA or saline placebo by IM injection.

Among participants who received ENFLONSIA or saline placebo, the median age of infants was 3.1 months (range: 0 to 12 months); 80% were less than 6 months; 16% were greater than or equal to 6 to less than 9 months, 4% were greater than or equal to 9 months of age, and 51% were male. Of these participants, 18% were GA greater than or equal to 29 weeks and less than 35 weeks, and 82% were GA greater than or equal to 35 weeks. The racial distribution was as follows: 45% were White; 27% were Asian; 14% were Black or African American; 12% were Multi-racial and 2% were American Indian or Alaska Native; 28% were of Hispanic or Latino ethnicity.

The primary endpoint was the incidence of RSV-associated Medically Attended Lower Respiratory Infection (MALRI) characterized as cough or difficulty breathing and requiring ≥1 indicator of LRI (wheezing, rales/crackles) or severity (chest wall in-drawing/retractions, hypoxemia, tachypnea, dehydration due to respiratory symptoms) through 150 days after dosing. Medically Attended (MA) includes all healthcare provider visits in settings such as outpatient clinic, clinical study site, emergency department, urgent care center, and/or hospital. The statistical criterion for success required the lower bound of the 95% CI of efficacy to be greater than 25%. RSV-associated hospitalization through 150 days after dosing was evaluated as a key secondary endpoint. The statistical criterion for success required the lower bound of the 95% CI of efficacy to be greater than 0%. Both efficacy endpoints required an RSV-positive RT-PCR nasopharyngeal (NP) sample.

Table 3 displays efficacy results for the primary and key secondary RSV-associated disease endpoints in preterm and full-term infants from days 1 through 150 post-dose.

Table 3: Incidence of RSV-Associated Disease in Infants Born at ≥29 Weeks GA Days 1 Through 150 Post-Dose (Trial 004)
RSV-Associated Endpoint | ENFLONSIA (n=2,411) |  | Placebo (n=1,203) |  | Efficacy [Efficacy for MALRI (requiring ≥1 indicator of LRI or severity) and hospitalization based on relative risk reduction against placebo adjusted for hemisphere at randomization, gestational age group and age group at randomization.] (95% CI) [Estimate and 95% CI of efficacy were estimated from the modified Poisson regression with robust variance method.]
RSV-Associated Endpoint | Number of cases | Incidence Rate over 5 months | Number of cases | Incidence Rate over 5 months | Efficacy [Efficacy for MALRI (requiring ≥1 indicator of LRI or severity) and hospitalization based on relative risk reduction against placebo adjusted for hemisphere at randomization, gestational age group and age group at randomization.] (95% CI) [Estimate and 95% CI of efficacy were estimated from the modified Poisson regression with robust variance method.]
MALRI (requiring ≥1 indicator of LRI or severity) | 60 | 0.026 | 74 | 0.065 | 60.5% (44.2, 72.0) [(p<0.001)]
Hospitalization | 9 | 0.004 | 28 | 0.024 | 84.3% (66.7, 92.6)
n=Number of participants eligible for inclusion in the full analysis set population.

14.3 Prevention of RSV-Associated Disease in Infants Born at ≤35 Weeks Gestational Age and Infants with CLD of Prematurity or Hemodynamically Significant CHD Entering Their First RSV Season (Trial 007)

Trial 007 is a Phase 3, randomized, partially-blind, palivizumab-controlled, multi-site trial conducted in 27 countries from the Northern and Southern Hemispheres to evaluate the efficacy of ENFLONSIA in early (<29 weeks GA) or moderate preterm infants (≥29 to ≤35 weeks GA), and infants with chronic lung disease of prematurity or congenital heart disease of any GA, who are at increased risk for severe RSV disease. Participants were randomized to receive ENFLONSIA or palivizumab by IM injection. Participants randomized to ENFLONSIA received a single 105 mg dose on Day 1 followed by a dose of placebo one month later; 15 mg/kg palivizumab was administered on Day 1 and every month thereafter for a total of 3 to 5 doses.

Among participants who received ENFLONSIA or palivizumab, the median age of infants was 2.5 months (range: 0 to 12 months); 89% were less than 6 months; 9% were greater than or equal to 6 to less than 9 months, 2% were greater than or equal to 9 months of age; and 50% were male. Of these participants, 28% had CLD, 11% had CHD, 6% were GA less than 29 weeks with neither CLD nor CHD and 55% were GA greater than or equal to 29 weeks with neither CLD nor CHD. The racial distribution was as follows: 52% were White; 18% were Asian; 15% were Black or African American; 12% were Multi-racial, and 1% were American Indian or Alaska Native; 32% were of Hispanic or Latino ethnicity.

The efficacy of ENFLONSIA in infants at increased risk for severe RSV disease, including preterm infants and infants with chronic lung disease of prematurity or congenital heart disease was established by extrapolation of efficacy of ENFLONSIA from Trial 004 to Trial 007 based on similar pharmacokinetic exposure [see Clinical Pharmacology (12.3)]. The incidence rate of RSV-associated MALRI (requiring ≥1 indicator of LRI or severity) through 150 days after dosing was generally comparable between ENFLONSIA (incidence rate=3.6%, 95% CI: 2.0, 6.0) and palivizumab (incidence rate=2.9%, 95% CI: 1.5, 5.2). The incidence rate of RSV-associated hospitalization through 150 days after dosing was generally comparable between ENFLONSIA (incidence rate=1.3%, 95% CI: 0.4, 2.9) and palivizumab (incidence rate=1.5%, 95% CI: 0.5, 3.2).

16 HOW SUPPLIED/STORAGE AND HANDLING

How Supplied

ENFLONSIA injection is a sterile, preservative-free, clear to slightly opalescent, colorless to slightly yellow solution supplied as follows:

Carton containing one or ten single-dose prefilled type I glass syringe(s) with Luer Lock and plunger stopper. The prefilled syringe is not made with natural rubber latex.

Prefilled syringe | Pack Size | NDC
105 mg/0.7 mL single-dose | Carton of 1 | 0006-5073-01
105 mg/0.7 mL single-dose | Carton of 10 | 0006-5073-02

Storage and Handling

- Store prefilled syringes under refrigeration at 36°F to 46°F (2°C to 8°C).
- Keep the prefilled syringe in the original carton to protect from light until time of use.
- ENFLONSIA may be kept at room temperature between 68°F to 77°F (20°C to 25°C) for a maximum of 48 hours. After removal from the refrigerator, ENFLONSIA must be used within 48 hours or discarded.
- Do not freeze. Do not shake.

17 PATIENT COUNSELING INFORMATION

Advise the child’s caregiver to read the FDA-approved patient labeling (Patient Information).

Hypersensitivity Reactions Including Anaphylaxis

Inform the patient’s caregiver of the signs and symptoms of potential hypersensitivity reactions, and advise the caregiver to seek medical attention immediately if the infant experiences a hypersensitivity reaction to ENFLONSIA [see Warnings and Precautions (5.1)].

Dosage and Administration

Advise the caregiver that the infant will receive ENFLONSIA by IM injection by a healthcare provider [see Dosage and Administration (2.1)].

Manufactured by:
Merck Sharp & Dohme LLC
Rahway, NJ 07065, USA

U.S. license number 0002

For patent information: www.msd.com/research/patent

Copyright © 2025 Merck & Co., Inc., Rahway, NJ, USA, and its affiliates.
All rights reserved.

uspi-mk1654-i-2506r001

Patient Information
ENFLONSIA™ (en-flahn-see-ah)
(clesrovimab-cfor)
injection, for intramuscular use

What is ENFLONSIA?
ENFLONSIA is a prescription medicine to help prevent lung disease, including severe lung disease, caused by Respiratory Syncytial Virus (RSV) in newborns and babies who are born during or entering their first RSV season.

ENFLONSIA contains antibodies to help prevent RSV disease.

It is not known if ENFLONSIA is safe and effective in children older than 12 months of age.

Your child should not receive ENFLONSIA if your child has a history of serious allergic reactions to any of the ingredients in ENFLONSIA. See the end of this Patient Information leaflet for a complete list of ingredients in ENFLONSIA.

Before your child receives ENFLONSIA, tell their healthcare provider about all of your child’s medical conditions, including if your child:

- is scheduled to have heart surgery during or entering their first RSV season.

Tell your child’s healthcare provider about all the medicines your child takes, including prescription and over-the-counter medicines, vitamins, and herbal supplements.

How is ENFLONSIA given?

- ENFLONSIA is given as an injection, in the thigh muscle, by your child’s healthcare provider.
- Your child should get ENFLONSIA before the start of or during the RSV season. RSV season is the time of year when RSV infections are most common, usually occurring fall through spring. Your child’s healthcare provider can tell you when the RSV season starts in your area.
- Your child may still get RSV disease after receiving ENFLONSIA. Talk to your child’s healthcare provider about what symptoms to look for.
- If your child has heart surgery, your child’s healthcare provider may need to give your child an additional ENFLONSIA injection soon after surgery.
- Your child can get ENFLONSIA at the same time as routine childhood vaccines.

What are the possible side effects of ENFLONSIA?

- Serious allergic reactions have happened with other medicines like ENFLONSIA. Get medical help right away if your child has any of the following signs or symptoms of a serious allergic reaction, including:

- swelling of the face, mouth, or tongue
- difficulty swallowing or breathing
- unresponsiveness

- bluish color of skin, lips or under fingernails
- muscle weakness
- severe rash, hives or itching

The most common side effects of ENFLONSIA are:

- redness and swelling at the site of your child’s injection
- rash

These are not all the possible side effects of ENFLONSIA.
Call your doctor for medical advice about side effects. You may report side effects to FDA at 1-800-FDA-1088.

General information about the safe and effective use of ENFLONSIA.
Medicines are sometimes prescribed for purposes other than those listed in a Patient Information leaflet. You can ask your pharmacist or child’s healthcare provider for information about ENFLONSIA that is written for health professionals.

What are the ingredients in ENFLONSIA?

Active ingredient: clesrovimab-cfor
Inactive ingredients: arginine hydrochloride, histidine, L-histidine monohydrochloride monohydrate, polysorbate 80, sucrose and water for injection.

Manufactured by: Merck Sharp & Dohme LLC, Rahway, NJ 07065, USA. U.S. License No. 0002

For patent information: www.msd.com/research/patent.

Copyright © 2025 Merck & Co., Inc., Rahway, NJ, USA, and its affiliates.
All rights reserved.

usppi-mk1654-i-2506r000

For more information, go to www.ENFLONSIA.com or call 1-877-888-4231.

This Patient Information has been approved by the U.S. Food and Drug Administration

Issued: 06/2025

PRINCIPAL DISPLAY PANEL - 1 Single-Dose Syringe Carton

NDC 0006-5073-01
One 105 mg/0.7 mL single-dose
prefilled syringe

ENFLONSIA™
(clesrovimab-cfor) Injection

105 mg / 0.7 mL

For Intramuscular Use Only
This package does not contain a needle.
Must be administered by a healthcare provider.

REFRIGERATE

Rx Only

PRINCIPAL DISPLAY PANEL - 10 Single-Dose Syringe Carton

NDC 0006-5073-02
Ten 105 mg/0.7 mL single-dose
prefilled syringes

ENFLONSIA™
(clesrovimab-cfor)
Injection

105 mg / 0.7 mL

For Intramuscular Use Only
This package does not contain needles.
Must be administered by a healthcare provider.

REFRIGERATE

Rx only

PRINCIPAL DISPLAY PANEL - 0.7 mL Syringe Label

NDC 0006-5073-99
One 105 mg/0.7 mL single-dose
prefilled syringe

ENFLONSIA™
(clesrovimab-cfor)
Injection

105 mg / 0.7 mL

For Intramuscular Use Only
Rx only

Store at 2°C-8°C (36°F-46°F).

Manuf. by: Merck Sharp & Dohme LLC
U.S. License No. 0002